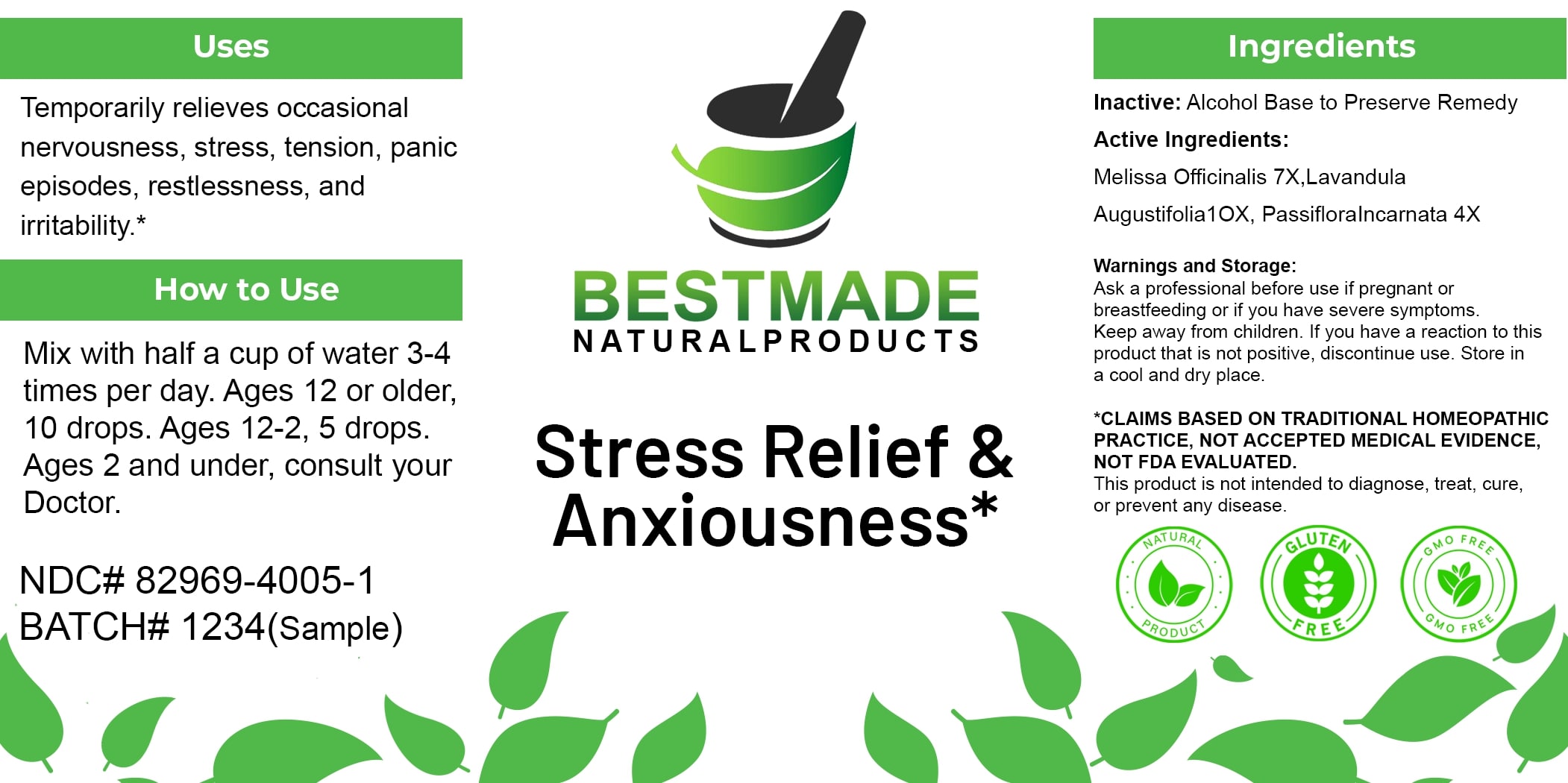 DRUG LABEL: Bestmade Natural Products Stress Relief and Anxiousness
NDC: 82969-4005 | Form: LIQUID
Manufacturer: Bestmade Natural Products
Category: homeopathic | Type: HUMAN OTC DRUG LABEL
Date: 20250307

ACTIVE INGREDIENTS: MELISSA OFFICINALIS WHOLE 7 [hp_X]/10 [hp_X]; LAVANDULA ANGUSTIFOLIA WHOLE 10 [hp_X]/10 [hp_X]; PASSIFLORA INCARNATA FLOWERING TOP 4 [hp_X]/10 [hp_X]
INACTIVE INGREDIENTS: ALCOHOL 10 [hp_X]/10 [hp_X]

Stress Relief & Anxiety Control

DOSAGE AND ADMINISTRATION

How to Use

Mix with half a cup of water 3-4 times per day. Ages 12 or older, 10 drops. Ages 12-2, 5 drops. Ages 2 and under, consult your Doctor.

INACTIVE INGREDIENT

Ingredients

Inactive: Alcohol Base to Preserve Remedy

ACTIVE INGREDIENT

Active Ingredients: Melissa Officinalis 7X, Lavandula Augustifolia 10X, Passiflora Incarnata 4X

Uses

Temporarily relieves occasional nervousness, stress, tension, panic episodes, restlessness, and irritability.*

*CLAIMS BASED ON TRADITIONAL HOMEOPATHIC PRACTICE, NOT ACCEPTED MEDICAL EVIDENCE, NOT FDA EVALUATED.

This product is not intended to diagnose, treat, cure, or prevent any disease.

Uses

Temporarily relieves occasional nervousness, stress, tension, panic episodes, restlessness, and irritability.*

*CLAIMS BASED ON TRADITIONAL HOMEOPATHIC PRACTICE, NOT ACCEPTED MEDICAL EVIDENCE, NOT FDA EVALUATED.

This product is not intended to diagnose, treat, cure, or prevent any disease.

Warnings and Storage:

Ask a professional before use if pregnant or breastfeeding or if you have severe symptoms. Keep away from children. If you have a reaction to this product that is not positive, discontinue use. Store in a cool and dry place.

*CLAIMS BASED ON TRADITIONAL HOMEOPATHIC PRACTICE, NOT ACCEPTED MEDICAL EVIDENCE, NOT FDA EVALUATED.

This product is not intended to diagnose, treat, cure, or prevent any disease.

KEEP OUT OF REACH OF CHILDREN

Warnings and Storage:

Ask a professional before use if pregnant or breastfeeding or if you have severe symptoms. Keep away from children. If you have a reaction to this product that is not positive, discontinue use. Store in a cool and dry place.

Entire package label